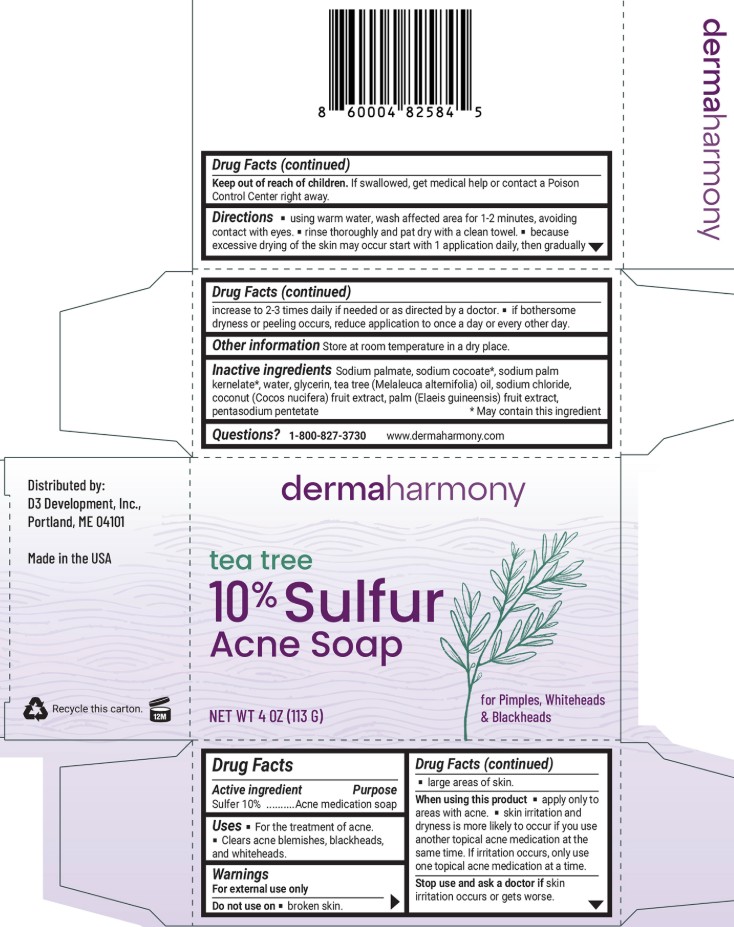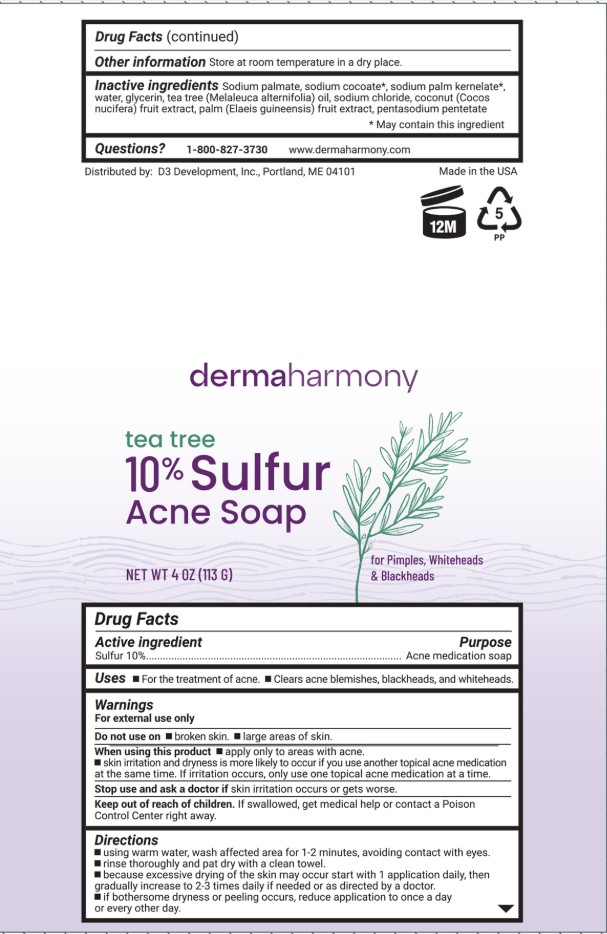 DRUG LABEL: Dermaharmony 10% Sulfur
NDC: 71819-015 | Form: SOAP
Manufacturer: D3 Development, Inc.
Category: otc | Type: HUMAN OTC DRUG LABEL
Date: 20251201

ACTIVE INGREDIENTS: SULFUR 10 g/100 g
INACTIVE INGREDIENTS: TEA TREE OIL; ELAEIS GUINEENSIS FRUIT; SODIUM CHLORIDE; SODIUM PALMATE; SODIUM PALM KERNELATE; SODIUM COCOATE; WATER; GLYCERIN; PENTASODIUM PENTETATE; COCONUT

Dermaharmony 10% Sulfur Soap with Tea Tree Oil

Drug Facts

Active ingredient

Sulfur 10%

Purpose

Acne medication soap

Uses

- For the treatment of acne.
- Clears acne blemishes, blackheads, and whiteheads.

Warnings

For external use only

Do not use on

- broken skin.
- large areas of the skin.

When using this product

- apply only to areas with acne.
- skin irritation and dryness is more likely to occur if you use another topical acne medication at the same time. If irritation occurs, only use one topical acne medication at a time.

Stop use and ask a doctor ifskin irritation occurs or gets worse.

Keep out of reach of children.If swallowed, get medical help or contact a Poison Control Center right away.

Directions

- using warm water, wash affected area for 1-2 minutes, avoiding contact with the eyes.
- rinse thoroughly and pat dry with a clean towel.
- because excessive drying of the skin may occur start with 1 application daily, then gradually increase to 2-3 times daily if needed or as directed by a doctor.
- if bothersome dryness or peeling occurs, reduce application to once a day or every other day.

STORAGE AND HANDLING

Other informationStore at room temperature in a dry place.

Inactive ingredients

Sodium palmate, sodium cocoate*, sodium palm kernelate*, water, glycerin, tea tree (Melaleuca alternifolia) oil, sodium chloride, coconut (Cocos nucifera) fruit extract, palm (Elaeis guineensis) fruit extract, pentasodium penetate

*May contain this ingredient

Questions?

1-800-827-3730www.dermaharmony.com

Distributed by: D3 Development, Inc., Portland, ME 04101

Made in USA

PACKAGE LABEL

dermaharmony

10% Sulfur SOAP with Tea Tree Oil

For Acne Pimples, Blackheads & Whiteheads

NET WT 4 OZ (113 G)